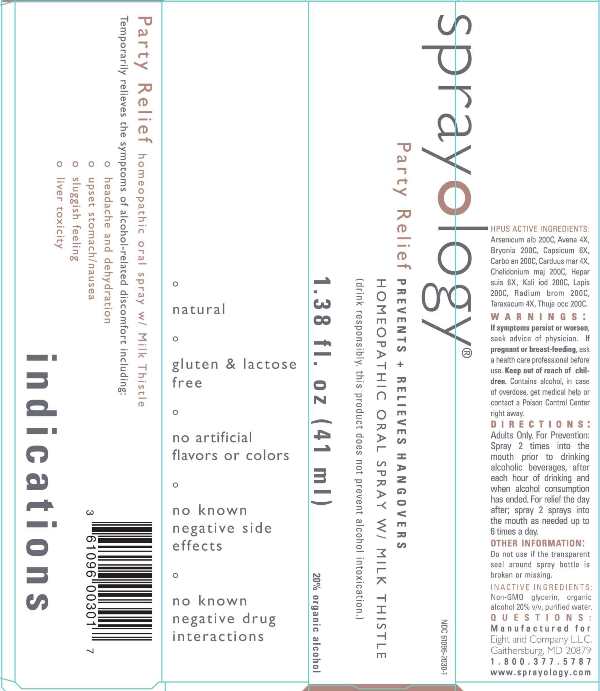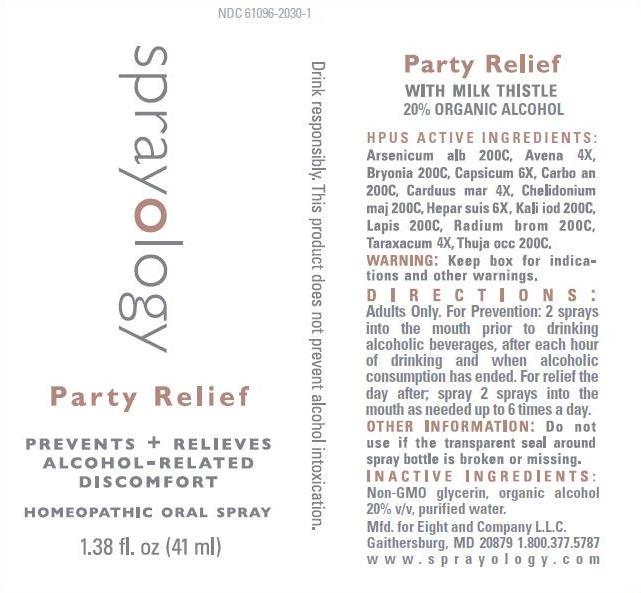 DRUG LABEL: Party Relief
NDC: 61096-2030 | Form: LIQUID
Manufacturer: Eight and Company L.L.C
Category: homeopathic | Type: HUMAN OTC DRUG LABEL
Date: 20251218

ACTIVE INGREDIENTS: ARSENIC TRIOXIDE 200 [hp_C]/41 mL; AVENA SATIVA FLOWERING TOP 4 [hp_X]/41 mL; BRYONIA ALBA ROOT 200 [hp_C]/41 mL; CAPSICUM 6 [hp_X]/41 mL; CARBO ANIMALIS 200 [hp_C]/41 mL; MILK THISTLE 4 [hp_X]/41 mL; CHELIDONIUM MAJUS WHOLE 200 [hp_C]/41 mL; PORK LIVER 6 [hp_X]/41 mL; POTASSIUM IODIDE 200 [hp_C]/41 mL; CALCIUM HEXAFLUOROSILICATE 200 [hp_C]/41 mL; RADIUM BROMIDE 200 [hp_C]/41 mL; TARAXACUM OFFICINALE 4 [hp_X]/41 mL; THUJA OCCIDENTALIS LEAFY TWIG 200 [hp_C]/41 mL
INACTIVE INGREDIENTS: GLYCERIN; ALCOHOL; WATER

Party Relief

ACTIVE INGREDIENTS:

Arsenicum Album 200C, Avena Sativa 4X, Bryonia (Alba) 200C, Capsicum Annuum 6X, Carbo Animalis 200C, Carduus Marianus 4X, Chelidonium Majus 200C, Hepar Suis 6X, Kali Iodatum 200C, Lapis Albus 200C, Radium Bromatum 200C, Taraxacum Officinale 4X, Thuja Occidentalis 200C.

PURPOSE:

Temporarily relieves the symptoms of alcohol-related discomfort including:

° headache and dehydration

° upset stomach/nausea

° sluggish feeling

° liver toxicity

WARNINGS:

If symptoms persist or worsen, seek advice of physician. If pregnant or breast-feeding, ask a health care professional before use. Keep out of reach of children. Contains alcohol, in case of overdose, get medical help or contact a Poison Control Center right away.

Keep out of reach of children. Contains alcohol, in case of overdose, get medical help or contact a Poison Control Center right away.

DIRECTIONS:

Adults Only. For Prevention: Spray 2 times into the mouth prior to drinking alcoholic beverages, after each hour of drinking and when alcohol consumption has ended.
For relief the day after: spray 2 sprays into the mouth as needed up to 6 times a day.

OTHER INFORMATION:

Do not use if the transparent seal around spray bottle is broken or missing.

INDICATIONS:

Temporarily relieves the symptoms of alcohol-related discomfort including:

° headache and dehydration

° upset stomach/nausea

° sluggish feeling

° liver toxicity

° natural

° gluten & lactose free

° no artifical flavors or colors

° no known negative side effects

° no known negative drug interactions

INACTIVE INGREDIENTS:

Non-GMO Glycerin, organic alcohol 20% v/v, purified water.

QUESTIONS:

Manufactured for Eight and Company L.L.C.

Gaithersburg, MD 20879 1.800.377.5787

www.sprayology.com

PACKAGE LABEL DISPLAY:

NDC 61096-2030-1

sprayology

Party Relief

PREVENTS + RELIEVES HANGOVERS

HOMEOPATHIC ORAL SPRAY W/ MILK THISTLE

[drink responsibly, this product does not prevent alcohol intoxication]

1.38 fl.oz (41 ml)